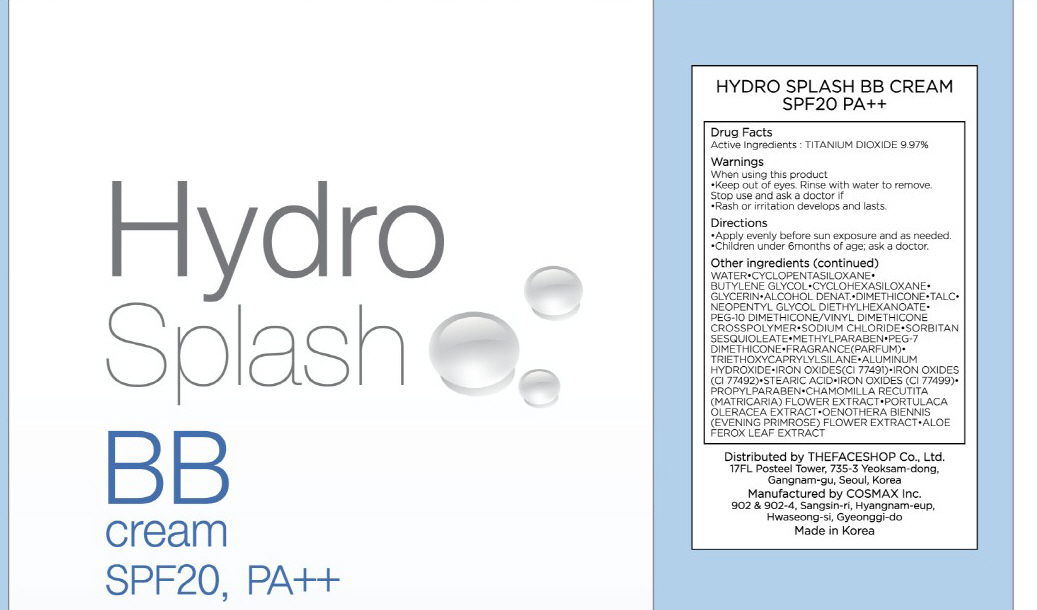 DRUG LABEL: HYDRO SPLASH BB
NDC: 51523-012 | Form: CREAM
Manufacturer: THEFACESHOP CO., LTD.
Category: otc | Type: HUMAN OTC DRUG LABEL
Date: 20100714

ACTIVE INGREDIENTS: TITANIUM DIOXIDE 4.48 g/45 g

Drug Facts

Active Ingredient: TITANIUM DIOXIDE

Inactive ingredients:
WATER, CYCLOPENTASILOXANE, BUTYLENE GLYCOL, CYCLOHEXASILOXANE, GLYCERIN, ALCOHOL DENAT., DIMETHICONE, TALC, NEOPENTYL GLYCOL DIETHYLHEXANOATE,
PEG-10 DIMETHICONE/VINYL DIMETHICONE CROSSPOLYMER, SODIUM CHLORIDE, SORBITAN SESQUIOLEATE, METHYLPARABEN, PEG-7 DIMETHICONE, FRAGRANCE, TRIETHOXYCAPRYLYLSILANE, ALUMINUM HYDROXIDE, IRON OXIDES(CI 77491), IRON OXIDES(CI 77492), STEARIC ACID, IRON OXIDES(CI 77499), PROPYLPARABEN, CHAMOMILLA RECUTITA (MATRICARIA) FLOWER EXTRACT, PORTULACA OLERACEA EXTRACT, OENOTHERA BIENNIS (EVENING PRIMROSE) FLOWER EXTRACT, ALOE FEROX LEAF EXTRACT

Warnings:
When using this product
Keep out of eyes. Rinse with water to remove.
Stop use and ask a doctor if
Rash or irritation develops and lasts.
Directions:
Apply evenly before sun exposure and as needed.
Children under 6months of age; ask a doctor.